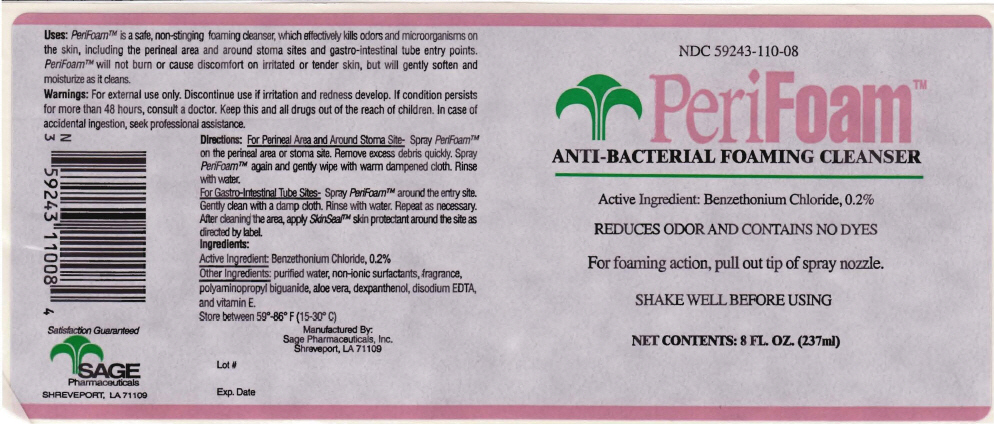 DRUG LABEL: Perifoam
NDC: 59243-110 | Form: SOLUTION
Manufacturer: Sage Pharmaceuticals, Inc.
Category: otc | Type: HUMAN OTC DRUG LABEL
Date: 20130802

ACTIVE INGREDIENTS: BENZETHONIUM CHLORIDE 2 mg/1 mL
INACTIVE INGREDIENTS: POLOXAMER 188; POLIHEXANIDE; WATER; ALOE VERA LEAF; TOCOPHERSOLAN; DECYL GLUCOSIDE; CAPRIC DIETHANOLAMIDE; EDETATE DISODIUM

Perifoam™

Uses

PURPOSE

PeriFoam™ is a safe, non-stinging foaming cleanser, which effectively kills odors and microorganisms on the skin, including the perineal area and around stoma sites and gastro-intestinal tube entry paints. PeriFoam™ will not bum or cause discomfort on irritated or tender skin, but will gently soften and moisturize as it cleans.

Warnings

For external use only. Discontinue use ~ irritation and redness develop.

ASK DOCTOR

If condition persists for more than 48 hours, consult a doctor.

KEEP OUT OF REACH OF CHILDREN

Keep this and all drugs out of the reach of children. In case of accidental ingestion, seek professional assistance.

Directions

For Perineal Area and Around Stoma Site

Spray PeriFoam™ on the perineal area or stoma site. Remove excess debris quickly. Spray PeriFoam™ again and gently wipe with water dampened cloth. Rinse with water:

For Gastro-Intestinal Tube Sites

Spray PeriFoam™ around the entry site. Gently clean with a damp cloth. Rinse with water. Repeat as necessary. After cleaning the area. Apply SkinSeal™skin protectant around the site as directed by label.

Ingredients

Active Ingredient

Benzethonium Chloride, 0.2

Other Ingredients

purified water, non-ionic surtactants, fragrance, polyaminopropyl biguanide, aloe vera, dexpanthenol, disodium EDTA, and vitamin E.

STORAGE AND HANDLING

Store between 59"-86" F (15-30°C)

Manufactured By:
Sage Pharmaceuticals, Inc.
Shreveport, LA 71109

PRINCIPAL DISPLAY PANEL - 237ml Bottle Label

NDC 59243-110-08

PeriFoam™
ANTI-BACTERIAL FOAMING CLEANSER

Active Ingredient: Benzethonium Chloride, 0.2%

REDUCES ODOR AND CONTAINS NO DYES

For foaming action, pull out tip of spray nozzle.

SHAKE WELL BEFORE USING

NET CONTENTS: 8 FL. OZ. (237ml)